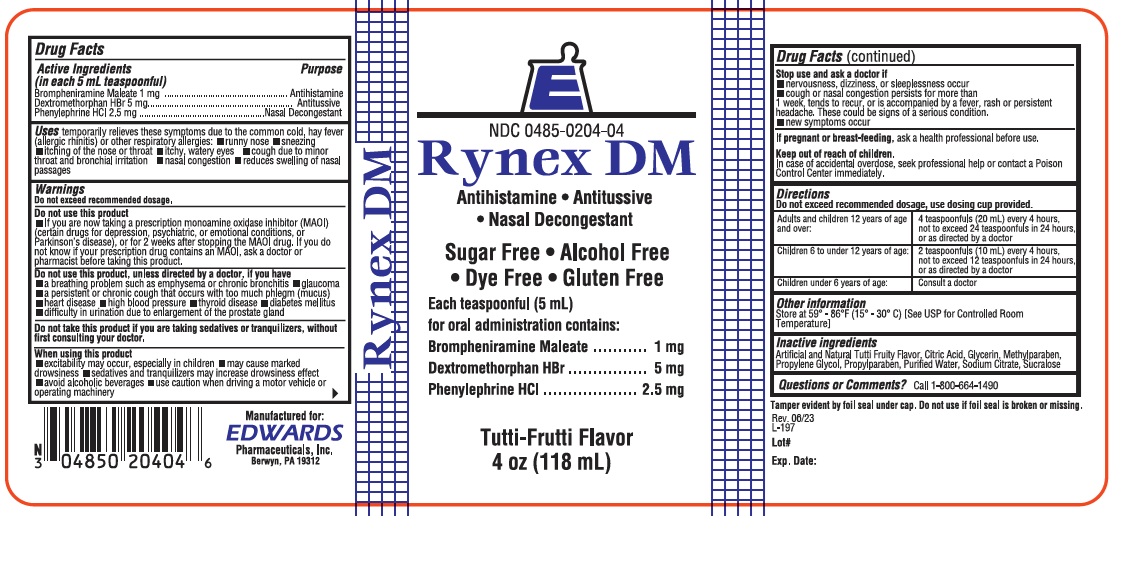 DRUG LABEL: Rynex
NDC: 0485-0204 | Form: LIQUID
Manufacturer: Edwards Pharmaceuticals, Inc
Category: otc | Type: HUMAN OTC DRUG LABEL
Date: 20251231

ACTIVE INGREDIENTS: PHENYLEPHRINE HYDROCHLORIDE 2.5 mg/5 mL; BROMPHENIRAMINE MALEATE 1 mg/5 mL; DEXTROMETHORPHAN HYDROBROMIDE 5 mg/5 mL
INACTIVE INGREDIENTS: CITRIC ACID MONOHYDRATE; GLYCERIN; PROPYLENE GLYCOL; WATER; SODIUM CITRATE, UNSPECIFIED FORM; SACCHARIN SODIUM; SORBITOL

Ed-RynexDM 0204

Drug Facts

Active ingredients
(in each 5 mL teaspoonful)
Brompheniramine Maleate 1mg
Dextromethorphan Hydrobromide 5 mg
Phenylephrine Hydrochloride 2.5 mg

Purpose

Antihistamine
Antitussive
Nasal Decongestant

Uses

temporarily relieves these symptoms due to the common cold, hay fever, (allergic rhinitis) or other upper respiratory allergies:

- runny nose
- sneezing
- itching of nose or throat
- itchy, watery eyes
- cough due to minor throat and bronchial irritation
- nasal congestion
- reduces swelling of nasal passages

Warnings

Do not exceed recommended dosage.

Do not use this product

- if you are now taking a prescription monoamine oxidase inhibitor (MAOI) (certain drugs for depression, psychiatric, or emotional conditions, or Parkinson's disease), or for 2 weeks after stopping the MAOI drug. If you do not know if your prescription drug contains an MAOI, ask a doctor or pharmacist before taking this product.

Ask a doctor before use if you have

- a breathing problem such as emphysema or chronic bronchitis
- glaucoma
- trouble urinating to to an enlarged prostate gland
- a cough that lasts or is chronic such as occurs with smoking, asthma or emphysema
- a cough that occurs with too much phlegm (mucus)
- heart disease
- high blood pressure
- thyroid disease
- diabetes

Ask a doctor or pharmacist before use if you are

taking sedatives or tranquilizers.

When using this product

- excitability may occur, especially in children
- may cause marked drowsiness
- avoid alcoholic drinks
- alcohol, sedatives, and tranquilizers may increase the drowsiness effect
- be careful when driving a motor vehicle or operating machinery

Stop use and ask a doctor if

- nervousness, dizziness, or sleeplessness occur
- cough or nasal congestion persists for more than 1 week, tends to recur, or is accompanied by a fever, rash or persistent headache. A persistent cough may be a sign of a serious condition.
- new symptoms occur

If pregnant or breast-feeding,

ask a health professional before use.

Keep out of the reach of children.

In case of overdose, get medical help or contact a Poison Control Center right away.

Directions

Do not exceed recommended dosage.

Adults and children 12 years of age and older: | 4 teaspoonfuls (20 mL) every 4 hours, not to exceed 24 teaspoonfuls in 24 hours.
Children 6 to under 12 years of age: | 2 teaspoonfuls (10 mL) every 4 hours, not to exceed 12 teaspoonfuls in 24 hours.
Children under 6 years of age: | Consult a doctor

Other information

Store at 59° - 86°F (15° - 30°C)

Inactive ingredients

Citric Acid, Glycerin, Propylene Glycol, Purified Water, Sodium Citrate, Sodium Saccharin, Sorbitol, Tutti Frutti Flavor.

Questions? Comments?

Call 1-800-664-1490

PRODUCT PACKAGING

The packaging below represents the labeling currently used:
Principal display panel and side panel for 473 mL label:
NDC 00485-0204-16
Rynex DM Liquid
ANTIHISTAMINE ∙ ANTITUSSIVE
NASAL DECONGESTANT
Each 5 mL (one teaspoonful) for oral administration contains:
Brompheniramine Maleate, USP..................1 mg
Dextromethorphan HBr, USP.......................5 mg
Phenylephrine HCl, USP...........................2.5 mg
ALCOHOL FREE ∙ DYE FREE
GLUTEN FREE ∙ SUGAR FREE
______________________________________________
FOR PROFESSIONAL USE ONLY
Tutti-Frutti Flavor
Manufactured for:
EDWARDS
Pharmaceuticals, Inc.
Ripley, MS 38663
16 fl oz (473 mL)
Tamper evident by foil seal under cap. Do not use if foil seal is broken or missing.
Dispense in a tight, light-resistant container with a child-resistant cap.
THIS BOTTLE IS NOT TO BE DISPENSED TO THE CONSUMER.
The labeling for this product includes professional labeling which is not
intended for use by the general public.
Manufactured for: Edwards Pharmaceuticals, Inc., Ripley, MS 38663
Iss. 01/12